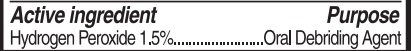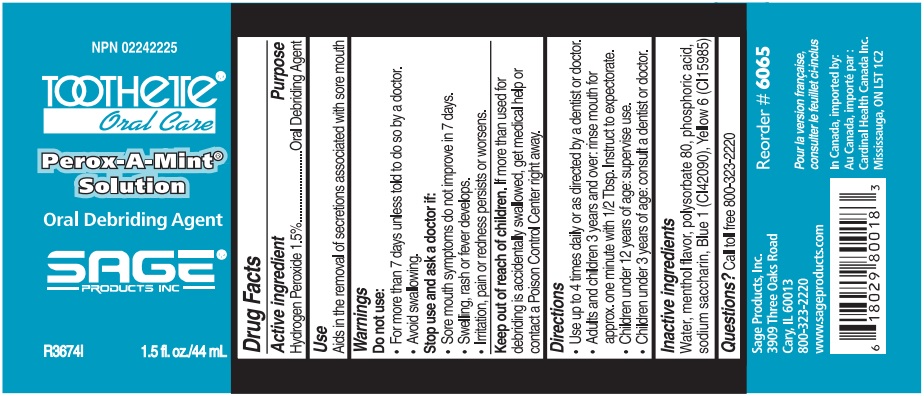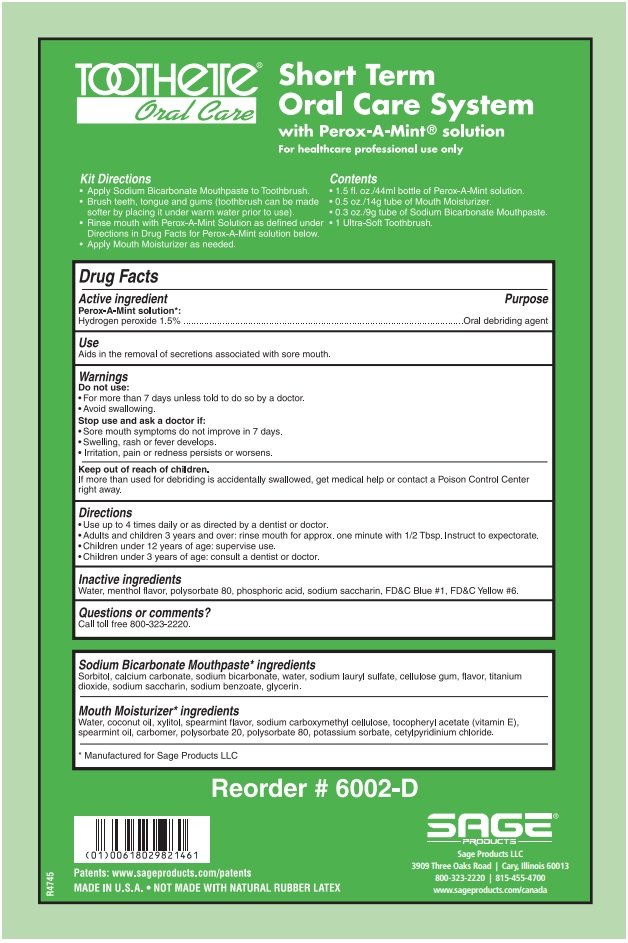 DRUG LABEL: Short Term Oral Care System
NDC: 53462-024 | Form: KIT | Route: BUCCAL
Manufacturer: Sage Products LLC
Category: otc | Type: HUMAN OTC DRUG LABEL
Date: 20190117

ACTIVE INGREDIENTS: HYDROGEN PEROXIDE 15 mg/1 mL
INACTIVE INGREDIENTS: WATER; PHOSPHORIC ACID; POLYSORBATE 80; SACCHARIN SODIUM; FD&C BLUE NO. 1; FD&C YELLOW NO. 6

Short Term Oral Care System

Use

Aids in the removal of secretions associated with sore mouth

Warnings

Do not use:

- For more than 7 days unless told to do so by a doctor.
- Avoid Swallowing.

Stop use and ask a doctor if:

- Sore mouth symptoms do not improve in 7 days.
- Swelling, rash or fever develops.
- Irritation, pain or redness persists or worsens.

Keep out of reach of children.

If more than used for debriding is accidentally swallowed, get medical help or contact a Poison Control Center right away.

Directions

- Use up to 4 times daily or as directed by a dentist or doctor.
- Adults and children 3 years and over: rinse mouth for approx. one minute with 1/2 Tbsp. Instruct to expectorate.
- Children under 12 yeras of age: supervise use.
- Children under 3 years of age: consult a dentist or doctor.

Inactive Ingredients

Water, menthol flavor, polysorbate 80, phosphoric acid, sodium saccharin, Blue 1 (CI42090), Yellow 6 (CI15985)

Questions

Call toll free 800-323-2220

MADE IN U.S.A.

NOT MADE WITH NATURAL RUBBER LATEX